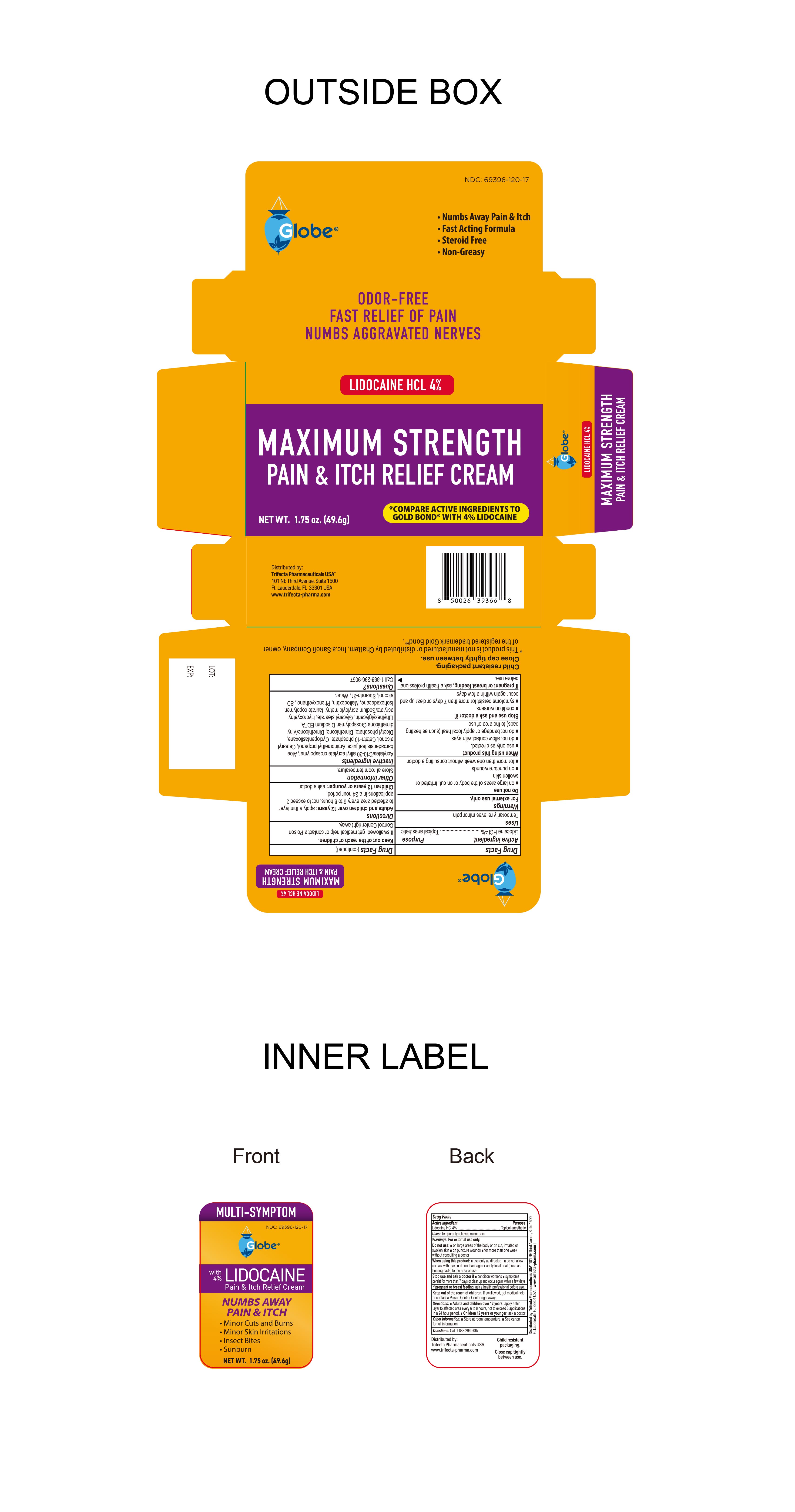 DRUG LABEL: Pain Itch Relief
NDC: 69396-120 | Form: CREAM
Manufacturer: Trifecta Pharmaceutical USA LLC
Category: otc | Type: HUMAN OTC DRUG LABEL
Date: 20241220

ACTIVE INGREDIENTS: LIDOCAINE HYDROCHLORIDE 4 g/100 g
INACTIVE INGREDIENTS: STEARETH-21; PHENOXYETHANOL; WATER; CYCLOMETHICONE 7; EDETATE DISODIUM ANHYDROUS; GLYCERYL MONOSTEARATE; DIMETHICONE/VINYL DIMETHICONE CROSSPOLYMER (HARD PARTICLE); MALTODEXTRIN; ISOHEXADECANE; AMINOMETHYLPROPANOL; CETOSTEARYL ALCOHOL; CETETH-10 PHOSPHATE; DIHEXADECYL PHOSPHATE; DIMETHICONE; ETHYLHEXYLGLYCERIN; HYDROXYETHYL ACRYLATE/SODIUM ACRYLOYLDIMETHYL TAURATE COPOLYMER (100000 MPA.S AT 1.5%); ALCOHOL; ALOE VERA LEAF; CARBOMER INTERPOLYMER TYPE A (55000 CPS)

Globe Maximum Strength Pain & Itch Relief Cream

Active Ingredient

Lidocaine HCI 4%

Purpose

Topical Anesthetic

Uses

Temporarily relieves minor pain

Warnings

For external use only.

When using this product

Use only as directed.

Do not allow contact with eyes.

Do not bandage or apply local heat such as heating pads to the area of use

Do Not Use

On large areas of the body or on cut, irritated or swollen skin

On puncture wounds

For more than one week without consulting a doctor

If Pregnant or Breast Feeding

Ask a health professional before use.

Stop Use and ask a Doctor if:

- Condition worsens
- symptoms persist for more than 7 days or clear up and occur again within a few days.

Keep out of Reach of Children

If swallowed, get medical help or contact a Poison Control Center right away

Directions

Adults and children over 12 years:

Apply a thin layer to affected area every 6 to 8 hours, not to exceed 3 applications in a 24 hour period.

Children 12 years or younger: ask a doctor

Questions

For Questions please call 1 888 296 9067

Other Information

Store at room temperature

Inactive Ingredient:

Cetostearyl alcohol, Ethylparaben, Glycerin, Glyceryl Sterate, Light Mineral Oil, Petrolatum, Polyoxyethylene Lauryl Ether, Purified Water, Sodium Lauryl Sulfate.

Distributed By

Trifecta Pharmaceuticals USA

101 NE Third Avenue, Suite 1500

Ft. Lauderdale, FL. 33301 USA

www.trifecta-pharma.com

This product is not manufactured or distributed by Chattem, Inc. a Sanofi Company owner of the registered trademark Gold Bond.